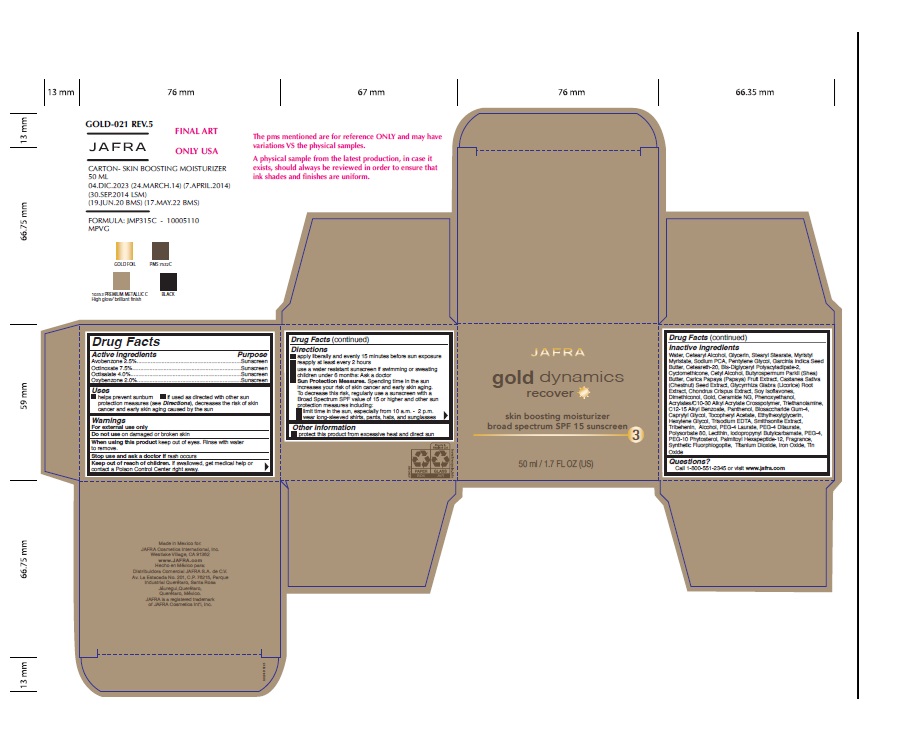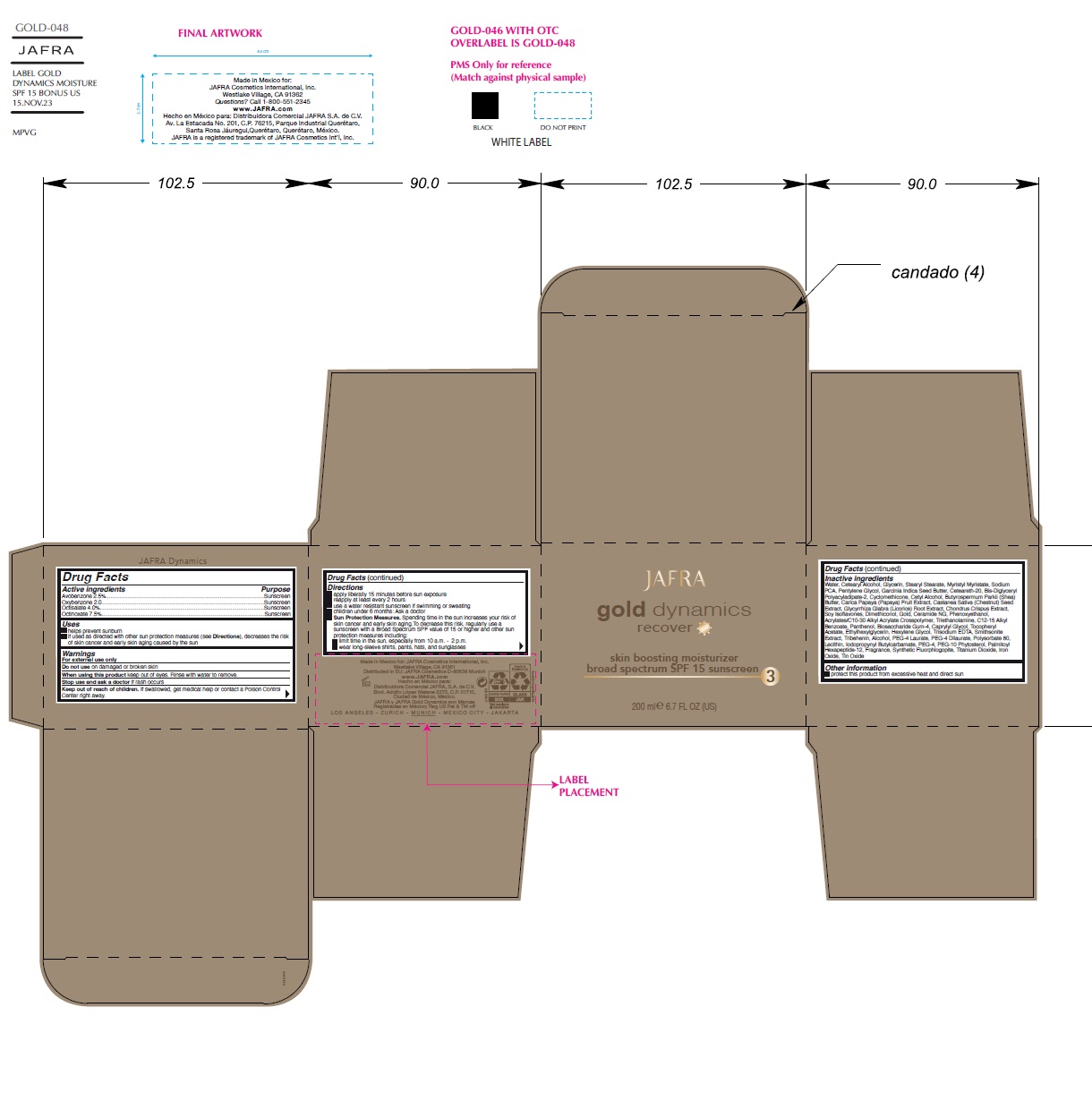 DRUG LABEL: Gold Dynamics Skin Boosting Moisturizer Broad Spectrum SPF 15 Sunscreen
NDC: 68828-099 | Form: CREAM
Manufacturer: Distribuidora Comercial Jafra, S.A. de C.V.
Category: otc | Type: HUMAN OTC DRUG LABEL
Date: 20251107

ACTIVE INGREDIENTS: AVOBENZONE 2.5 g/100 mL; OXYBENZONE 2 g/100 mL; OCTISALATE 4 g/100 mL; OCTINOXATE 7.5 g/100 mL
INACTIVE INGREDIENTS: WATER; CETOSTEARYL ALCOHOL; GLYCERIN; STEARYL STEARATE; MYRISTYL MYRISTATE; SODIUM PYRROLIDONE CARBOXYLATE; PENTYLENE GLYCOL; GARCINIA INDICA SEED BUTTER; POLYOXYL 20 CETOSTEARYL ETHER; BIS-DIGLYCERYL POLYACYLADIPATE-2; CYCLOMETHICONE; CETYL ALCOHOL; SHEA BUTTER; PAPAYA; SPANISH CHESTNUT; GLYCYRRHIZA GLABRA; CHONDRUS CRISPUS CARRAGEENAN; SOY ISOFLAVONES; DIMETHICONOL (100000 CST); GOLD; CERAMIDE NG; PHENOXYETHANOL; CARBOMER COPOLYMER TYPE B (ALLYL PENTAERYTHRITOL CROSSLINKED); TROLAMINE; ALKYL (C12-15) BENZOATE; PANTHENOL; BIOSACCHARIDE GUM-4; CAPRYLYL GLYCOL; .ALPHA.-TOCOPHEROL ACETATE; ETHYLHEXYLGLYCERIN; HEXYLENE GLYCOL; EDETATE TRISODIUM; TRIBEHENIN; ALCOHOL; PEG-4 LAURATE; PEG-4 DILAURATE; POLYSORBATE 80; LECITHIN, SOYBEAN; IODOPROPYNYL BUTYLCARBAMATE; POLYETHYLENE GLYCOL 200; PALMITOYL HEXAPEPTIDE-12; MAGNESIUM POTASSIUM ALUMINOSILICATE FLUORIDE; TITANIUM DIOXIDE; FERROUS OXIDE; STANNIC OXIDE

Active ingredient

Avobenzone 2.5%, Oxybenzone 2%, Octisalate 4%, Octinoxate 7.5%

Purpose

Sunscreen

Uses

- helps prevent sunburn
- if used as directed with other sun protection measures (see Directions), decreases the risk of skin cancer and early skin aging caused by the sun

Warnings

For external use only
Do not use on damaged or broken skin
When using this product keep out of eyes. Rinse with water to remove.
Stop use and ask a doctor if rash occurs
Keep out of reach of children.If swallowed, get medical help or contact a Poison Control Center right away.

Direction

• Apply liberally and evenly 15 minutes before sun exposure
• Reapply at least every 2 hours
• Use a water resistant sunscreen if swimming or sweating
• Children under 6 months of age: Ask a doctor
• Sun Protection Measures. Spending time in the sun increases your risk of skin cancer and early skin aging. To decrease this risk, regularly use a sunscreen with a Broad Spectrum SPF value of 15 or higher and other sun protection measures including:
• limit your time in the sun, especially from 10 a.m. – 2 p.m.
• wear long-sleeved shirts, pants, hats, and sunglasses

Other information

protect this product from excessive heat and direct sun

Inactive ingredients

Water, Cetearyl Alcohol, Glycerin, Stearyl Stearate, Myristyl Myristate, Sodium PCA, Pentylene Glycol, Garcinia Indica Seed Butter, Ceteareth-20, Bis-Diglyceryl Polyacyladipate-2, Cyclomethicone, Cetyl Alcohol, Butyrospermum Parkii (Shea) Butter, Carica Papaya (Papaya) Fruit Extract, Castanea Sativa (Chestnut) Seed Extract, Glycyrrhiza Glabra (Licorice) Root Extract, Chondrus Crispus Extract, Soy Isoflavones, Dimethiconol, Gold, Ceramide NG, Phenoxyethanol, Acrylates/C10-30 Alkyl Acrylate Crosspolymer, Triethanolamine, C12-15 Alkyl Benzoate, Panthenol, Biosaccharide Gum-4, Caprylyl Glycol, Tocopheryl Acetate, Ethylhexylglycerin, Hexylene Glycol, Trisodium EDTA, Smithsonite Extract, Tribehenin, Alcohol, PEG-4 Laurate, PEG-4 Dilaurate, Polysorbate 80, Lecithin, Iodopropynyl Butylcarbamate, PEG-4, PEG-10 Phytosterol, Palmitoyl Hexapeptide-12, Fragrance, Synthetic Fluorphlogopite, Titanium Dioxide, Iron Oxides, Tin Oxide

Questions?

Call 1-800-551-2345 or visit www.jafra.com